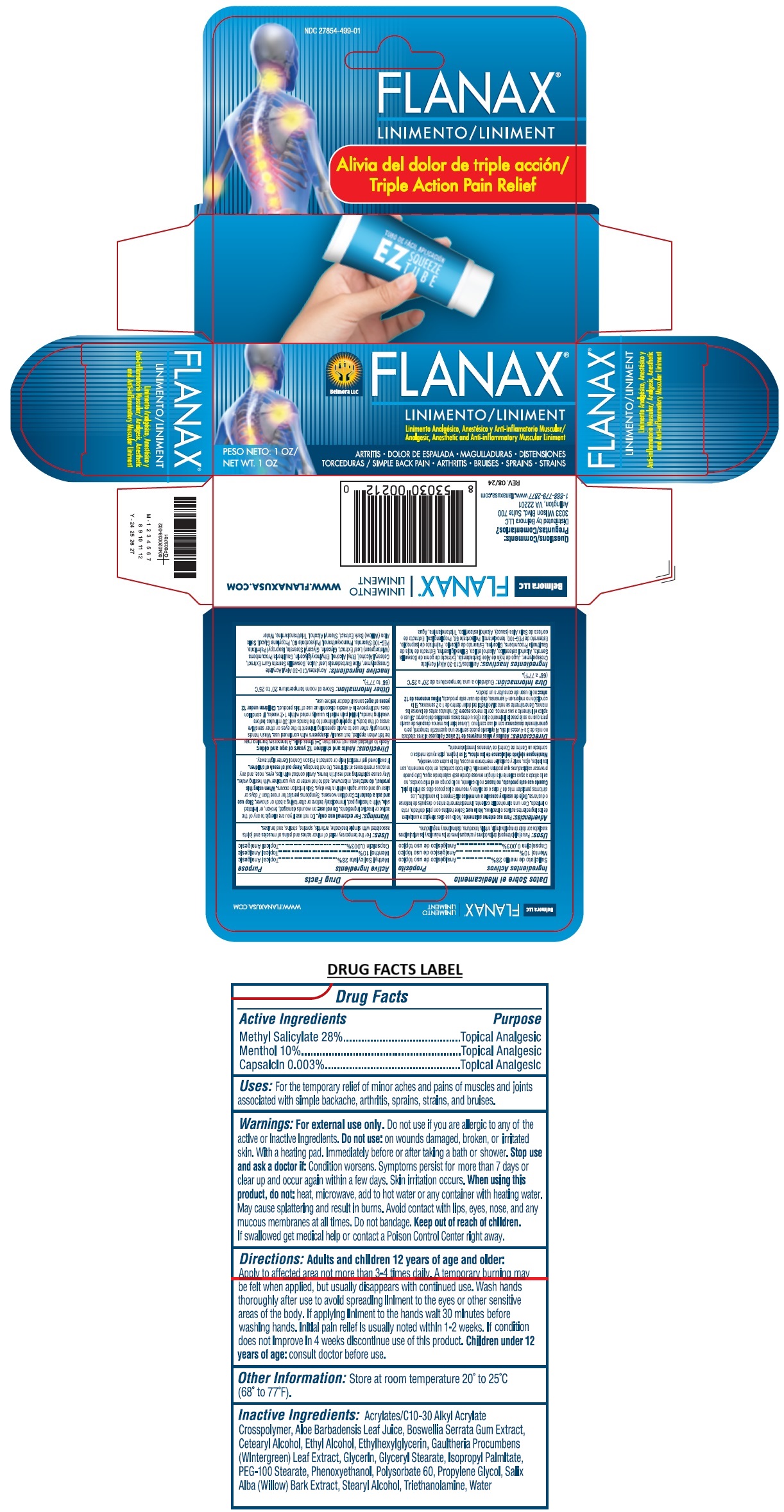 DRUG LABEL: FLANAX
NDC: 27854-499 | Form: LINIMENT
Manufacturer: Belmora LLC
Category: otc | Type: HUMAN OTC DRUG LABEL
Date: 20240813

ACTIVE INGREDIENTS: METHYL SALICYLATE 28 g/100 g; MENTHOL, UNSPECIFIED FORM 10 g/100 g; CAPSAICIN 0.003 g/100 g
INACTIVE INGREDIENTS: ACRYLATES/C10-30 ALKYL ACRYLATE CROSSPOLYMER (60000 MPA.S AT 0.5%); ALOE VERA LEAF; INDIAN FRANKINCENSE; CETOSTEARYL ALCOHOL; ALCOHOL; ETHYLHEXYLGLYCERIN; GAULTHERIA PROCUMBENS LEAF; GLYCERIN; GLYCERYL MONOSTEARATE; ISOPROPYL PALMITATE; PEG-100 MONOSTEARATE; PHENOXYETHANOL; POLYSORBATE 60; PROPYLENE GLYCOL; SALIX ALBA BARK; STEARYL ALCOHOL; TROLAMINE; WATER

FLANAX® LINIMENT

Active Ingredients

Methyl Salicylate 28%
Menthol 10%
Capsaicin 0.003%

Purpose

Topical Analgesic

Uses:

For the temporary relief of minor aches and pains of muscles and joints associated with simple backache, arthritis, sprains, strains, and bruises.

Warnings:

For external use only. Do not use if you are allergic to any of the active or inactive ingredients. Do not use: on wounds damaged, broken, or irritated skin. With a heating pad. Immediately before or after taking a bath or shower. Stop use and ask a doctor if: Condition worsens. Symptoms persist for more than 7 days or clear up and occur again within a few days. Skin irritation occurs. When using this product, do not: heat, microwave, add to hot water or any container with heating water. May cause splattering and result in burns. Avoid contact with lips, eyes, nose, and any mucous membranes at all times. Do not bandage.

Keep out of reach of children. If swallowed get medical help or contact a Poison Control Center right away.

Directions:

Adults and children 12 years of age and older: Apply to affected area not more than 3-4 times daily. A temporary burning may be felt when applied, but usually disappears with continued use. Wash hands thoroughly after use to avoid spreading liniment to the eyes or other sensitive areas of the body. If applying liniment to the hands wait 30 minutes before washing hands. Initial pain relief is usually noted within 1-2 weeks. If condition does not improve in 4 weeks discontinue use of this product. Children under 12 years of age: consult doctor before use.

Other Information:

Store at room temperature 20° to 25°C (68° to 77°F).

Inactive Ingredients:

Acrylates/C10-30 Alkyl Acrylate Crosspolymer, Aloe Barbadensis Leaf Juice, Boswellia Serrata Gum Extract, Cetearyl Alcohol, Ethyl Alcohol, Ethylhexylglycerin, Gaultheria Procumbens (Wintergreen) Leaf Extract, Glycerin, Glyceryl Stearate, Isopropyl Palmitate, PEG-100 Stearate, Phenoxyethanol, Polysorbate 60, Propylene Glycol, Salix Alba (Willow) Bark Extract, Stearyl Alcohol, Triethanolamine, Water

Analgesic, Anesthetic and Anti-inflammatory Muscular Liniment

Triple Action Pain Relief

Questions/Comments:
Distributed by Belmora LLC
3033 Wilson Blvd. Suite 700
Arlington, VA 22201
1-888-779-2877

WWW.FLANAXUSA.COM